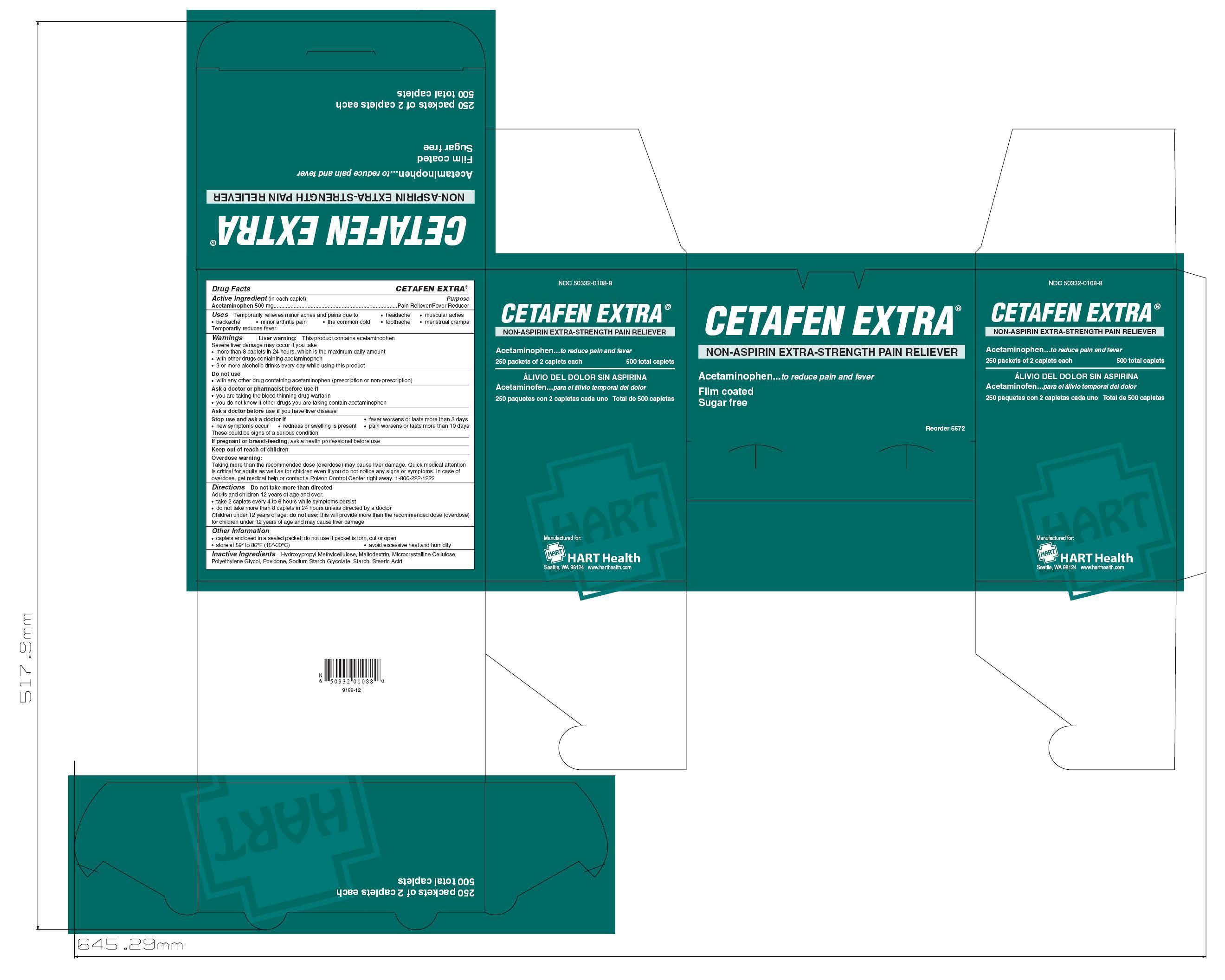 DRUG LABEL: CETAFEN EXTRA
NDC: 50332-0108 | Form: TABLET
Manufacturer: HART Health
Category: otc | Type: HUMAN OTC DRUG LABEL
Date: 20121111

ACTIVE INGREDIENTS: ACETAMINOPHEN 500 mg/1 1
INACTIVE INGREDIENTS: HYDROXYPROPYL METHYLCELLULOSE E5 [II]; MALTODEXTRIN; CELLULOSE, MICROCRYSTALLINE; PROPYLENE GLYCOL; POVIDONE; STEARIC ACID

CETAFEN EXTRA

Active Ingredient (in each caplet): Acetaminophen 500mg

Purpose: Pain Reliever / Fever Reducer

INDICATIONS AND USAGE

Uses: Temporarily relieves minor aches and pains due to:

- headache
- muscular aches
- backache
- minor arthritis pain
- the common cold
- toothache
- menstrual cramps

Temporarily reduces fever

WARNINGS

Warning: Liiver warning: This product contains acetaminophen. Severe liver damage may occur if you take

- more than 8 caplets in 24 hours, which is the maximum daily amount
- with other drugs containing acetaminophen
- 3 or more alcoholic drinks every day while using this product

Do not use with any other drug containing acetaminophen (prescription or non-prescription)

Ask a doctor or pharmacist before use if

- you are taking the blood thinning drug warfarin
- you do not know if other drugs you are taking contain acetaminophen

Ask a doctor before use if you have liver disease

Stop use and ask a doctor if

- new symptms occur
- redness or swelling is present
- fever worsens or lasts more than 3 days
- pain worsens or lasts more than 10 days

These could be signs of a serious condition

PREGNANCY OR BREAST FEEDING

If pregnant or breast-feeding, ask a health professional before use

Keep out of reach of children

OVERDOSAGE

Overdose warning: Taking more than the recommended dose (overdose) may cause liver damage. Quick medical attention is critical for adults as well as for children even if you do not notice any signs or symptoms. In case of overdose, get medical help or contact a Poison Control Center right away. 1-800-222-1222.

DOSAGE AND ADMINISTRATION

Directions: do not take more than directed

- Adults and children 12 years of age and over:
- take 2 caplets every 4 to 6 hours while symptoms persist
- do not take more than 8 caplets in 24 hours unless directed by a doctor

Children under 12 years of age: do not use; this will provide more than the recommended dose (overdose) for children under 12 years of age and may cause liver damage.

INACTIVE INGREDIENT

Inactive Ingredients: Hydroxypropyl Methylcellulose, Maltodextrin, Microcrystalline Cellulose, Polyethylene Glycol, Povidone, Sodium Starch Glycolate, Starch, Stearic Acid